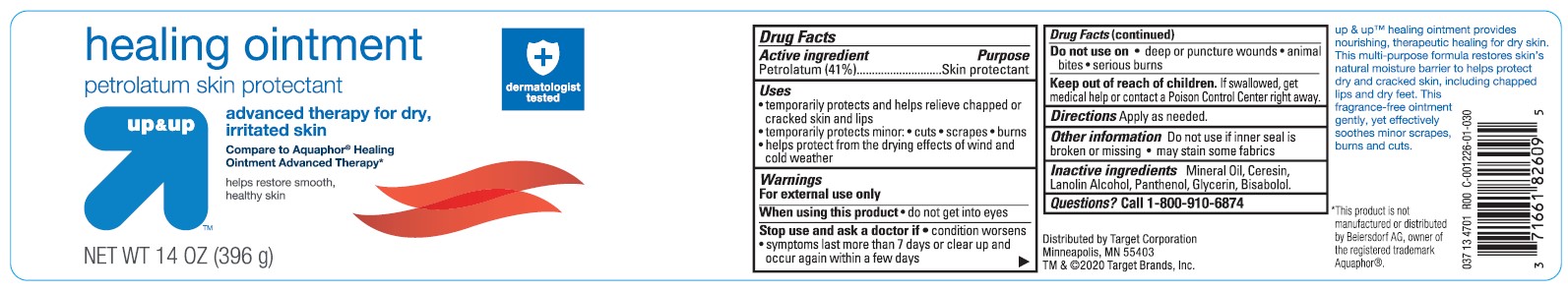 DRUG LABEL: Target Up and Up Healing Petrolatum Skin Protectant
NDC: 11673-234 | Form: OINTMENT
Manufacturer: TARGET CORPORATION
Category: otc | Type: HUMAN OTC DRUG LABEL
Date: 20241014

ACTIVE INGREDIENTS: PETROLATUM 410 mg/1 g
INACTIVE INGREDIENTS: MINERAL OIL; LANOLIN ALCOHOLS; PANTHENOL; GLYCERIN; .ALPHA.-BISABOLOL, (+/-)-; CERESIN

Target Up &Up Healing Ointment Petrolatum Skin Protectant

Active ingredient

Petrolatum (41%)

Purpose

Skin protectant

Uses

- temporarily protects and helps relieve chapped or cracked skin and lips
- temporarily protects minor:

• cuts

• scrapes

• burns

- helps protect from the drying effects of wind and cold weather

Warnings

For external use only

When using this product

• do not get into eyes

Stop use and ask a doctor if

• condition worsens • symptoms last more than 7 days or clear up and occur again within a few days

Do not use on

• deep or puncture wounds • animal bites • seriuos burns

Keep out of reach of children.

If swallowed, get medical help or contact a Poison Control Center right away.

Directions

Apply as needed.

Other information

- Do not use if inner seal is broken or missing
- may stain some fabrics

Inactive Ingredients

Mineral Oil, Ceresin, Lanolin Alcohol, Panthenol, Glycerin, Bisabolol.